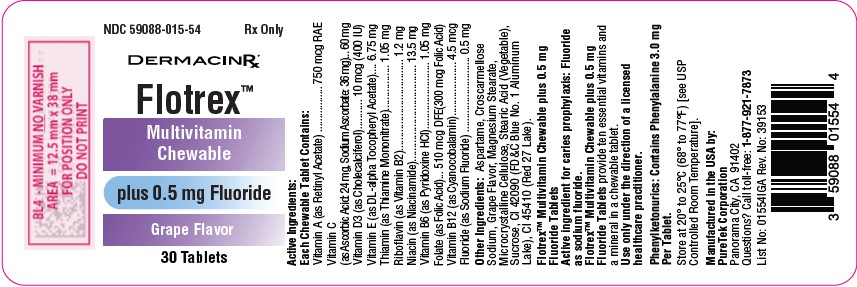 DRUG LABEL: Flotrex
NDC: 59088-015 | Form: TABLET, CHEWABLE
Manufacturer: PureTek Corporation
Category: prescription | Type: HUMAN PRESCRIPTION DRUG LABEL
Date: 20250714

ACTIVE INGREDIENTS: SODIUM FLUORIDE 0.5 mg/1 1; VITAMIN A 750 ug/1 1; ASCORBIC ACID 24 mg/1 1; SODIUM ASCORBATE 36 mg/1 1; CHOLECALCIFEROL 10 ug/1 1; .ALPHA.-TOCOPHEROL ACETATE, DL- 6.75 mg/1 1; THIAMINE MONONITRATE 1.05 mg/1 1; RIBOFLAVIN 1.2 mg/1 1; NIACINAMIDE 13.5 mg/1 1; PYRIDOXINE HYDROCHLORIDE 1.05 mg/1 1; FOLIC ACID 300 ug/1 1; CYANOCOBALAMIN 4.5 ug/1 1
INACTIVE INGREDIENTS: SUCROSE; CROSCARMELLOSE SODIUM; D&C RED NO. 27; FD&C BLUE NO. 1; MAGNESIUM STEARATE; CELLULOSE, MICROCRYSTALLINE; STEARIC ACID; ASPARTAME

Flotrex (0.5 mg Fluoride)
Prescribing Information

DESCRIPTION:

Active Ingredients:

Each Chewable Tablet Contains:

Vitamin A (as Retinyl Acetate) ........................................................... 750 mcg RAE
Vitamin C (as Ascorbic Acid: 24 mg, Sodium Ascorbate: 36 mg) ................. 60 mg
Vitamin D3 (as Cholecalciferol) .................................................... 10 mcg (400 IU)
Vitamin E (as DL-alpha Tocopheryl Acetate) .............................................. 6.75 mg
Thiamin (as Thiamine Mononitrate) ........................................................... 1.05 mg
Riboflavin (as Vitamin B2) ........................................................................... 1.2 mg
Niacin (as Niacinamide) ............................................................................ 13.5 mg
Vitamin B6 (as Pyridoxine HCl) ................................................................. 1.05 mg
Folate (as Folic Acid)....................................... 510 mcg DFE (300 mcg Folic Acid)
Vitamin B12 (as Cyanocobalamin) ............................................................. 4.5 mcg
Fluoride (as Sodium Fluoride) ..................................................................... 0.5 mg

Flotrex™ Multivitamin Chewable plus 0.5 mg Fluoride Tablets

Active ingredient for caries prophylaxis: Fluoride as sodium fluoride.

Flotrex™ Multivitamin Chewable plus 0.5 mg Fluoride Tablets provide fluoride and ten essential vitamins in a chewable tablet.

Other Ingredients: Aspartame, Croscarmellose Sodium, Grape Flavor, Magnesium Stearate, Microcrystalline Cellulose, Stearic Acid (Vegetable), Sucrose, CI 42090 (FD&C Blue No. 1 Aluminum Lake), CI 45410 (Red 27 Lake).

Phenylketonurics: Contains Phenylalanine 3.0 mg Per Tablet.

CLINICAL PHARMACOLOGY

It is well established that fluoridation of the water supply (1 ppm fluoride) during the period of tooth development leads to a significant decrease in the incidence of dental caries.

Flotrex™ Multivitamin Chewable plus 0.5 mg Fluoride Tablets provide sodium fluoride and ten essential vitamins in a chewable tablet. Because the tablets are chewable, they provide a topical as well as systemic source of fluoride. Hydroxyapatite is the principal crystal for all calcified tissue in the human body. The fluoride ion reacts with the hydroxyapatite in the tooth as it is formed to produce the more caries-resistant crystal, fluorapatite. The reaction may be expressed by the equation:

Ca10(PO4)6(OH) 2 + 2F^- ------- Ca10(PO4)6F 2 + 2OH^-

(Hydroxyapatite) (Fluorapatite)

Three stages of fluoride deposition in tooth enamel can be distinguished:

1. Small amounts (reflecting the low levels of fluoride in tissue fluids) are incorporated into the enamel crystals while they are being formed.

2. After enamel has been laid down, fluoride deposition continues in the surface enamel. Diffusion of fluoride from the surface inward is apparently restricted.

3. After eruption, the surface enamel acquires fluoride from the water, food, supplementary fluoride and smaller amounts from saliva.

INDICATIONS AND USAGE

This prescription chewable tablet is indicated for the prevention and treatment of vitamin and fluoride deficiencies in patients at high risk for dental caries and inadequate dietary intake of essential vitamins. It is specifically formulated to support normal growth and development, promote bone and dental health, and aid in the maintenance of overall metabolic and immune function.

Contraindications:

This product is contraindicated in patients with a known hypersensitivity to any of the ingredients.

The American Academy of Pediatrics recommends that children up to the age 16, in areas where drinking water contains less than optimal levels of fluoride, receive daily fluoride supplementation.

Flotrex™ Multivitamin Chewable plus 0.5 mg Fluoride Tablets provide 0.50 mg fluoride in tablet form for children 6-16 years of age in areas where the drinking water fluoride level is less than 0.3 ppm.

Flotrex™ Multivitamin Chewable plus 0.5 mg Fluoride Tablets supply significant amounts of Vitamins A, C, D, E, thiamine, riboflavin, niacin, vitamin B6, vitamin B12, and folate to supplement the diet, and to help assure that nutritional deficiencies of these vitamins will not develop. Thus, in a single easy-to-use preparation, children obtain ten essential vitamins and the important mineral, fluoride.

Children using Flotrex™ Multivitamin Chewable plus 0.5 mg Fluoride Tabletsregularly should receive semiannual dental examinations. The regular brushing of teeth and attention to good oral hygiene practices are also essential.

Flotrex™ Multivitamin Chewable plus 0.5 mg Fluoride Tablets is a prescription product for the clinical dietary management of the metabolic processes of caries prophylaxis and provides supplementation of the diet with ten essential vitamins.

WARNING

Keep out of the reach of children. In case of accidental overdose, seek professional assistance or contact a Poison Control Center immediately.

Caution:Do not eat or drink dairy products within one hour of fluoride administration.

Should be chewed. This product, as all chewable tablets, is not recommended for children under age 4 due to risk of choking.

PRECAUTION

The suggested dose of Flotrex™ Multivitamin Chewable plus 0.5 mg Fluoride Tablets should not be exceeded, since dental fluorosis may result from continued ingestion of large amounts of fluoride. Before prescribing Flotrex™ Multivitamin Chewable plus 0.5 mg Fluoride Tablets:

1. Determine the fluoride content of the drinking water from all major sources.

2. Make sure the child is not receiving significant amounts of fluoride from other sources such as medications and swallowed toothpaste.

3. Periodically check to make sure that the child does not develop significant dental fluorosis.

Folate in doses above 0.1 mg daily may obscure pernicious anemia, in that hematologic remission can occur while neurological manifestations remain progressive.There is a potential danger in administering folate to patients with undiagnosed anemia, since folate may obscure the diagnosis of pernicious anemia by alleviating the hematologic manifestations of the disease while allowing the neurologic complications to progress. This may result in severe nervous system damage before the correct diagnosis is made. Adequate doses of vitamin B12 may prevent, halt, or improve the neurologic changes caused by pernicious anemia. The patient’s medical conditions and consumption of other drugs, herbs, and/or supplements should be considered.

ADVERSE REACTIONS

Folate: Allergic sensitization has been reported following both oral and parenteral administration of folate. Adverse reactions have been reported with specific vitamins and minerals but generally at levels substantially higher than those contained herein. However, allergic and idiosyncratic reactions are possible at lower levels.

DOSAGE AND ADMINISTRATION

One tablet daily, to be dissolved in the mouth or chewed before swallowing. Do not give a chewable tablet to a child younger than 4 years old.

HOW SUPPLIED

Flotrex™ Multivitamin Chewable plus 0.5 mg Fluoride Tablets are purple-colored, grape-flavored, unscored tablets available by prescription only in bottles of 30 tablets. (NDC: 59088-015-54). Dispense in a tight, light-resistant container with a child-resistant closure, as defined in the USP/NF. All prescription substitutions using this product shall be pursuant to applicable state statutes. This is not an Orange Book product.

STORAGE

Do not use if bottle seal is broken.

Store at controlled room temperature 20° to 25°C (68° to 77°F).

[See USP Controlled Room Temperature].

Flotrex™ Multivitamin Chewable plus 0.5 mg Fluoride Tablets

Manufactured in the USA by:

PureTek Corporation

Panorama City, CA 91402

Questions? Call toll-free: 1-877-921-7873